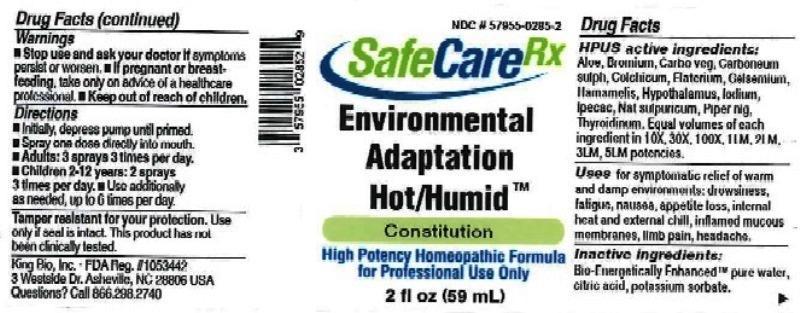 DRUG LABEL: Environmental Adaptation Hot and Humid
NDC: 57955-0285 | Form: LIQUID
Manufacturer: King Bio Inc.
Category: homeopathic | Type: HUMAN OTC DRUG LABEL
Date: 20161122

ACTIVE INGREDIENTS: ALOE 10 [hp_X]/59 mL; BROMINE 10 [hp_X]/59 mL; ACTIVATED CHARCOAL 10 [hp_X]/59 mL; CARBON DISULFIDE 10 [hp_X]/59 mL; COLCHICUM AUTUMNALE BULB 10 [hp_X]/59 mL; ECBALLIUM ELATERIUM FRUIT 10 [hp_X]/59 mL; GELSEMIUM SEMPERVIRENS ROOT 10 [hp_X]/59 mL; HAMAMELIS VIRGINIANA ROOT BARK/STEM BARK 10 [hp_X]/59 mL; BOS TAURUS HYPOTHALAMUS 10 [hp_X]/59 mL; IODINE 10 [hp_X]/59 mL; IPECAC 10 [hp_X]/59 mL; SODIUM SULFATE 10 [hp_X]/59 mL; GREEN PEPPERCORN 10 [hp_X]/59 mL; THYROID, UNSPECIFIED 10 [hp_X]/59 mL
INACTIVE INGREDIENTS: WATER; ANHYDROUS CITRIC ACID; POTASSIUM SORBATE

Environmental Adaptation Hot and Humid™

ACTIVE INGREDIENT

Drug Facts__________________________________________________________________________________________________________

HPUS active ingredients: Aloe socotrina, Bromium, Carbo vegetabilis, Carboneum sulphuratum, Colchicum autumnale, Elaterium, Gelsemium sempervirens, Hamamelis virginiana, Hypothalamus, Iodum, Ipecacuanha, Natrum sulphuricum, Piper nigrum, Thyroidinum. Equal volumes of each ingredient in 10X, 30X, 100X, 1LM, 2LM, 3LM and 5LM potencies.

INDICATIONS AND USAGE

Uses for symptomatic relief of warm and damp environments: drowsiness, fatigue, nausea, appetite loss, internal heat and external chill, inflamed mucus membranes, limb pain, headache.

Inactive Ingredients:

Bio-Energetically Enhanced™ pure water, citric acid and potassium sorbate.

Warnings

- Stop use and ask your doctor if symptoms persist or worsen.
- If pregnant or breast-feeding, take only on advice of a healthcare professional.

- Keep out of reach of children.

Directions

- Initially, depress pump until primed.
- Spray one dose directly into mouth.
- Adults 12 and up: 3 sprays 3 times per day.
- Children 2-12 years: 2 sprays 3 times per day.
- Use additionally as needed, up to 6 times per day.

OTHER SAFETY INFORMATION

Tamper resistant for your protection. Use only if safety seal is intact. This product has not been clinically tested.

PURPOSE

Uses for symptomatic relief of warm and damp environments:

- drowsiness
- fatigue
- nausea
- appetite loss
- internal heat and external chill
- inflamed mucus membranes
- limb pain
- headache